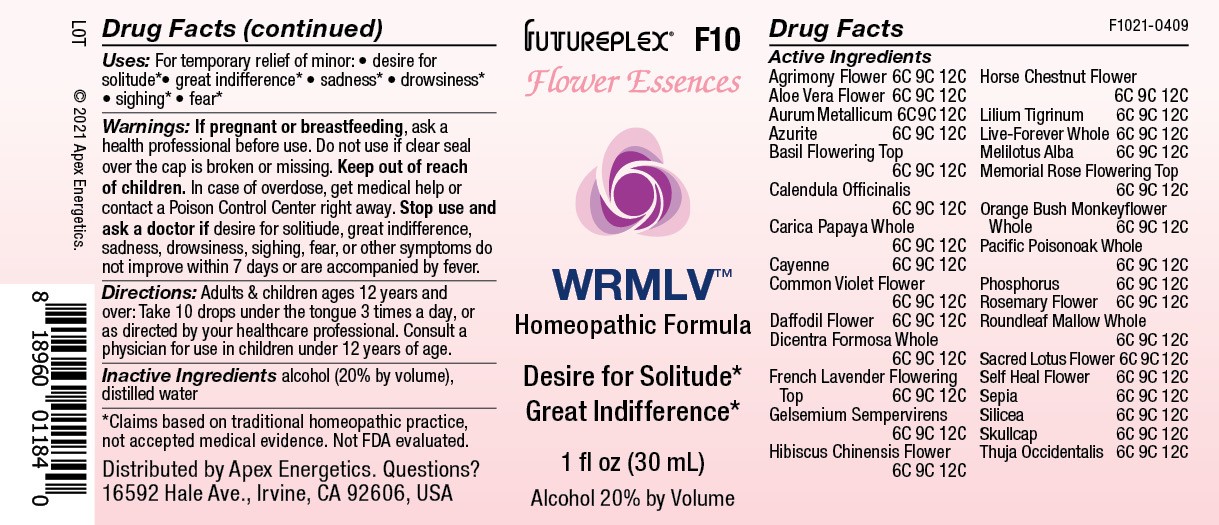 DRUG LABEL: F10
NDC: 63479-0610 | Form: SOLUTION/ DROPS
Manufacturer: Apex Energetics Inc.
Category: homeopathic | Type: HUMAN OTC DRUG LABEL
Date: 20240108

ACTIVE INGREDIENTS: LAVANDULA STOECHAS FLOWERING TOP 12 [hp_C]/1 mL; LILIUM LANCIFOLIUM WHOLE FLOWERING 12 [hp_C]/1 mL; DIPLACUS AURANTIACUS WHOLE 12 [hp_C]/1 mL; MELILOTUS ALBUS TOP 12 [hp_C]/1 mL; ROSA LUCIAE FLOWERING TOP 12 [hp_C]/1 mL; PHOSPHORUS 12 [hp_C]/1 mL; AZURITE 12 [hp_C]/1 mL; GELSEMIUM SEMPERVIRENS ROOT 12 [hp_C]/1 mL; ABELMOSCHUS MOSCHATUS FLOWER 12 [hp_C]/1 mL; AESCULUS HIPPOCASTANUM FLOWER 12 [hp_C]/1 mL; ROSMARINUS OFFICINALIS FLOWER 12 [hp_C]/1 mL; NELUMBO NUCIFERA FLOWER 12 [hp_C]/1 mL; SEPIA OFFICINALIS JUICE 12 [hp_C]/1 mL; SILICON DIOXIDE 12 [hp_C]/1 mL; SCUTELLARIA LATERIFLORA TOP 12 [hp_C]/1 mL; THUJA OCCIDENTALIS LEAFY TWIG 12 [hp_C]/1 mL; HYLOTELEPHIUM TELEPHIUM WHOLE 12 [hp_C]/1 mL; TOXICODENDRON DIVERSILOBUM WHOLE 12 [hp_C]/1 mL; CALENDULA OFFICINALIS FLOWERING TOP 12 [hp_C]/1 mL; CARICA PAPAYA WHOLE 12 [hp_C]/1 mL; NARCISSUS PSEUDONARCISSUS FLOWER 12 [hp_C]/1 mL; DICENTRA FORMOSA WHOLE 12 [hp_C]/1 mL; CAPSICUM 12 [hp_C]/1 mL; VIOLA ODORATA FLOWER 12 [hp_C]/1 mL; ALOE VERA FLOWER 12 [hp_C]/1 mL; GOLD 12 [hp_C]/1 mL; OCIMUM BASILICUM FLOWERING TOP 12 [hp_C]/1 mL; AGRIMONIA EUPATORIA FLOWER 12 [hp_C]/1 mL; MALVA NEGLECTA WHOLE 12 [hp_C]/1 mL; PRUNELLA VULGARIS FLOWER 12 [hp_C]/1 mL
INACTIVE INGREDIENTS: ALCOHOL; WATER

F10

Active Ingredients
Agrimony Flower | 6C 9C 12C
Aloe Vera Flower | 6C 9C 12C
Aurum Metallicum | 6C 9C 12C
Azurite | 6C 9C 12C
Basil Flowering Top | 6C 9C 12C
Calendula Officinalis | 6C 9C 12C
Carica Papaya Whole | 6C 9C 12C
Cayenne | 6C 9C 12C
Common Violet Flower | 6C 9C 12C
Daffodil Flower | 6C 9C 12C
Dicentra Formosa Whole | 6C 9C 12C
French Lavender Flowering Top | 6C 9C 12C
Gelsemium Sempervirens | 6C 9C 12C
Hibiscus Chinensis Flower | 6C 9C 12C
Horse Chestnut Flower | 6C 9C 12C
Lilium Tigrinum | 6C 9C 12C
Live-Forever Whole | 6C 9C 12C
Melilotus Alba | 6C 9C 12C
Memorial Rose Flowering Top | 6C 9C 12C
Orange Bush Monkeyflower Whole | 6C 9C 12C
Pacific Poisonoak Whole | 6C 9C 12C
Phosphorus | 6C 9C 12C
Rosemary Flower | 6C 9C 12C
Roundleaf Mallow Whole | 6C 9C 12C
Sacred Lotus Flower | 6C 9C 12C
Self Heal Flower | 6C 9C 12C
Sepia | 6C 9C 12C
Silicea | 6C 9C 12C
Skullcap | 6C 9C 12C
Thuja Occidentalis | 6C 9C 12C

INDICATIONS AND USAGE

Uses:

For temporary relief of minor:

desire for solitude*

great indifference*

sadness*

drowsiness*

sighing*

fear*

*Claims based on traditional homeopathic practice, not accepted medical evidence. Not FDA evaluated.

Warnings:

PREGNANCY OR BREAST FEEDING

If pregnant or breastfeeding, ask a health professional before use.

Do not use if clear seal over the cap is broken or missing.

Keep out of reach of children. In case of overdose, get medical help or contact a Poison Control Center right away.

Stop use and ask a doctor if desire for solitiude, great indifference, sadness, drowsiness, sighing, fear, or other symptoms do not improve within 7 days or are accompanied by fever.

Directions:

Adults & children ages 12 years and over: Take 10 drops under the tongue 3 times a day, or as directed by your healthcare professional. Consult a physician for use in children under 12 years of age.

Inactive Ingredients

alcohol (20% by volume), distilled water

Distributed by Apex Energetics. Questions?

16592 Hale Ave., Irvine, CA 92606, USA

PACKAGE LABEL

FUTUREPLEX® F10

Flower Essences

WRMLV™

Homeopathic Formula

Desire for Solitude*

Great Indifference*

1 fl oz (30 mL)

Alcohol 20% by Volume